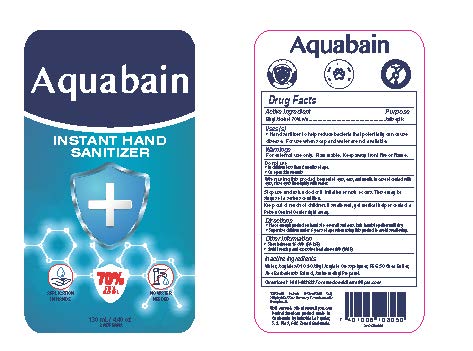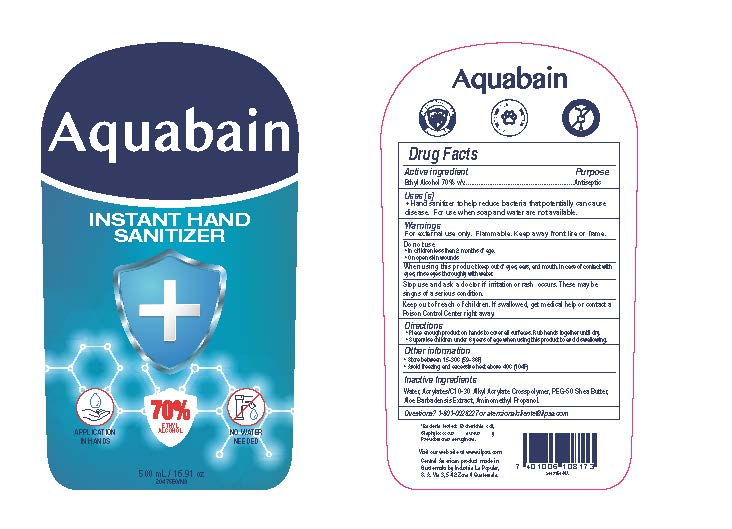 DRUG LABEL: Aquabain Instant Hand Sanitizer
NDC: 62476-005 | Form: GEL
Manufacturer: Industria La Popular, S.A.
Category: otc | Type: HUMAN OTC DRUG LABEL
Date: 20241202

ACTIVE INGREDIENTS: ALCOHOL 91 mL/130 mL
INACTIVE INGREDIENTS: AMINOMETHYL PROPANEDIOL; (C10-C30)ALKYL METHACRYLATE ESTER; PEG-50 SHEA BUTTER; ALOE VERA LEAF; WATER

Aquabain Instant Hand Sanitizer

Active Ingredient(s)

Ethyl Alcohol 70% v/v. Purpose: Antiseptic

Purpose

Antiseptic

Use

Hand Sanitizer to help reduce bacteria that potentially can cause disease. For use when soap and water are not available.

Warnings

For external use only. Flammable. Keep away from heat or flame

Do not use

- in children less than 2 months of age
- on open skin wounds

When using this product keep out of eyes, ears, and mouth. In case of contact with eyes, rinse eyes thoroughly with water.

Stop use and ask a doctor if irritation or rash occurs. These may be signs of a serious condition.

Keep out of reach of children. If swallowed, get medical help or contact a Poison Control Center right away.

Directions

- Place enough product on hands to cover all surfaces. Rub hands together until dry.
- Supervise children under 6 years of age when using this product to avoid swallowing.

Other information

- Store between 15-30C (59-86F)
- Avoid freezing and excessive heat above 40C (104F)

Inactive ingredients

Water, Acrylates/C10-30 Alkyl Acrylate Crosspolymer, PEG-50 Shea Butter, Aloe Barbadensis Extract, Aminomethyl Propanol